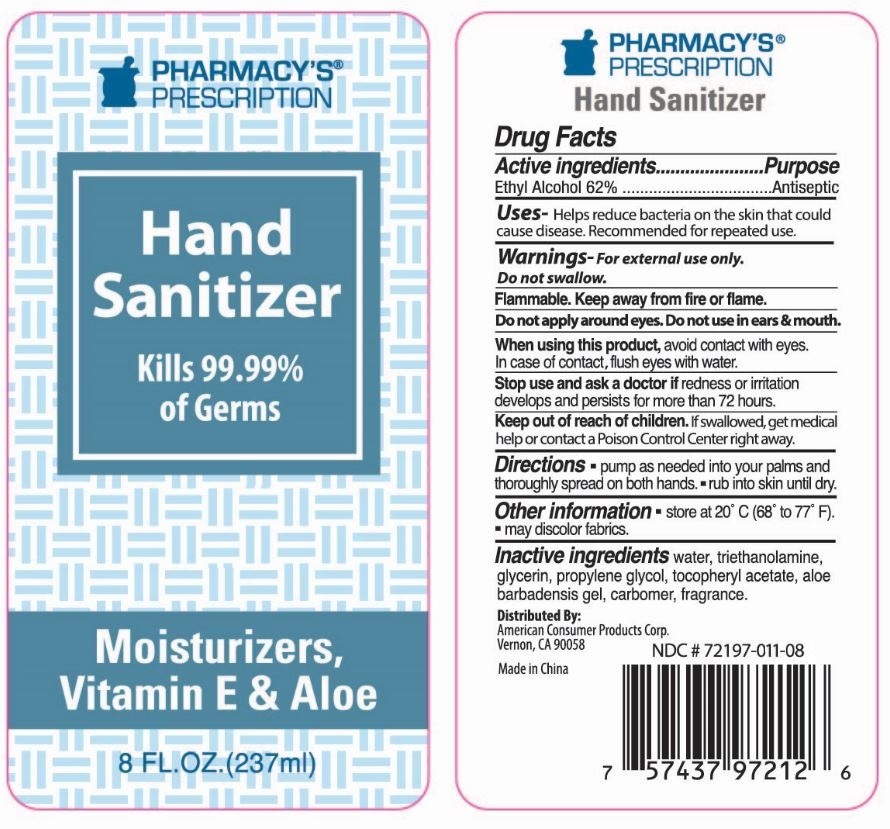 DRUG LABEL: PHARMACYS PRESCRIPTION 8OZ HAND SANITIZER
NDC: 72197-011 | Form: GEL
Manufacturer: American Consumer Products Corp
Category: otc | Type: HUMAN OTC DRUG LABEL
Date: 20250123

ACTIVE INGREDIENTS: ALCOHOL 62 mL/100 mL
INACTIVE INGREDIENTS: WATER; ALOE ARBORESCENS WHOLE; .ALPHA.-TOCOPHEROL ACETATE, D-; GLYCERIN; PROPYLENE GLYCOL 2-(2-METHYLBUTYRATE); CARBOMER HOMOPOLYMER TYPE C; TRIETHANOLAMINE 2-CYCLOHEXYL-4,6-DINITROPHENOLATE

Pharmacy's Prescription 8OZ Hand Sanitizer

Active Ingredient

Active Ingredients: Ethyl Alcohol 62%

Purpose

Purpose: Antiseptic

Uses - Helps reduce bacteria on the skin that could cause disease. Recommended for repeated use.

Warnings

Warnings - For external use only. Do not swallow.

Flammable. Keep away from fire or flame.

Do not apply around eyes. Do not use in ears & mouth.

Stop Use

Stop use and ask a doctor if: If redness or irritation develops and persists for more than 72 hours.

Keep out of reach of children. If swallowed, get medical help or contact a Poison Control Center right away.

Inactive Ingredients

Inactive ingredients - water, triethanolamine, glycerin, propylene glycol, tocopheryl acetate, aloe barbadensis gel, carbomer, fragrance.

Directions

Directions - pump as needed into your palms and thoroughly spread on both hands.- rub into skin until dry.

Indications & Usage Section

When using this product, avoid contact with eyes. In case of contact, flush eyes with water.

Other Information

Other Information - store at 20o C (68o to 77o F).

- may discolor fabrics.